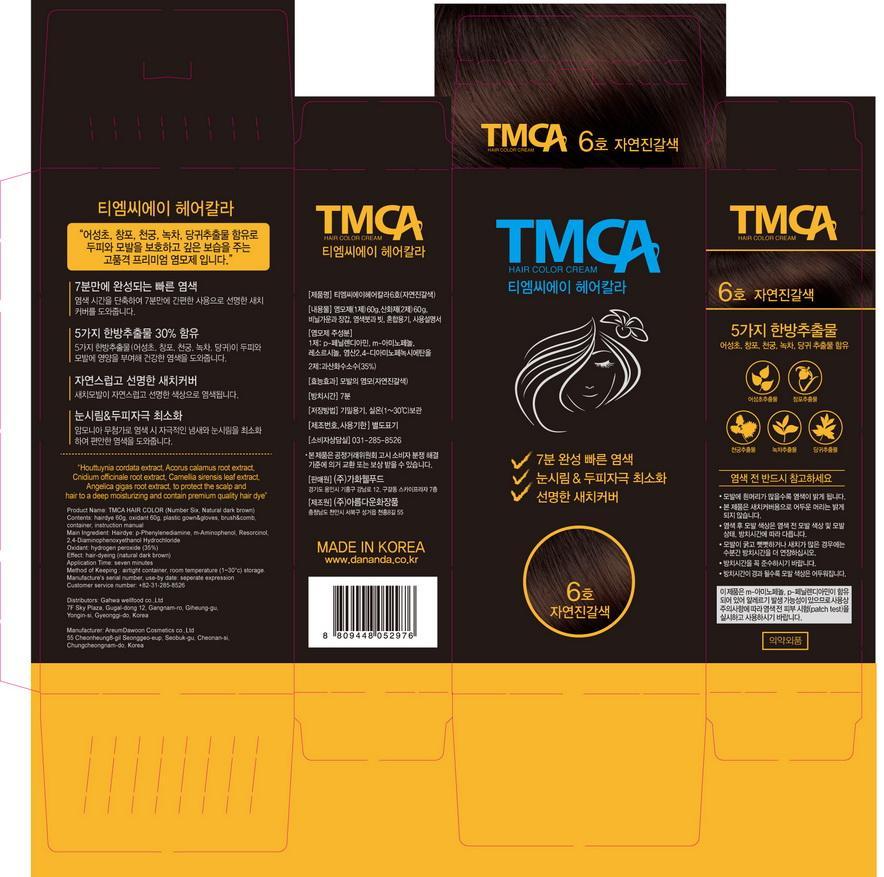 DRUG LABEL: TMCA HAIR COLOR Number Six (Natural dark brown)
NDC: 69100-3001 | Form: LIQUID
Manufacturer: Gahwa Well Food Co.,Ltd
Category: otc | Type: HUMAN OTC DRUG LABEL
Date: 20150903

ACTIVE INGREDIENTS: P-PHENYLENEDIAMINE 1.6 g/100 g
INACTIVE INGREDIENTS: WATER; ASCORBIC ACID

Drug Facts

ACTIVE INGREDIENT

p-phenylenediamine

INACTIVE INGREDIENT

water, resorcinol, ascorbic acid, stearic acid etc.

PURPOSE

hair coloring

keep out of reach of the children

INDICATIONS AND USAGE

apply to the hair and leave about 7 minutes and wash away with water

WARNINGS

do not sallow

DOSAGE AND ADMINISTRATION

for external use only